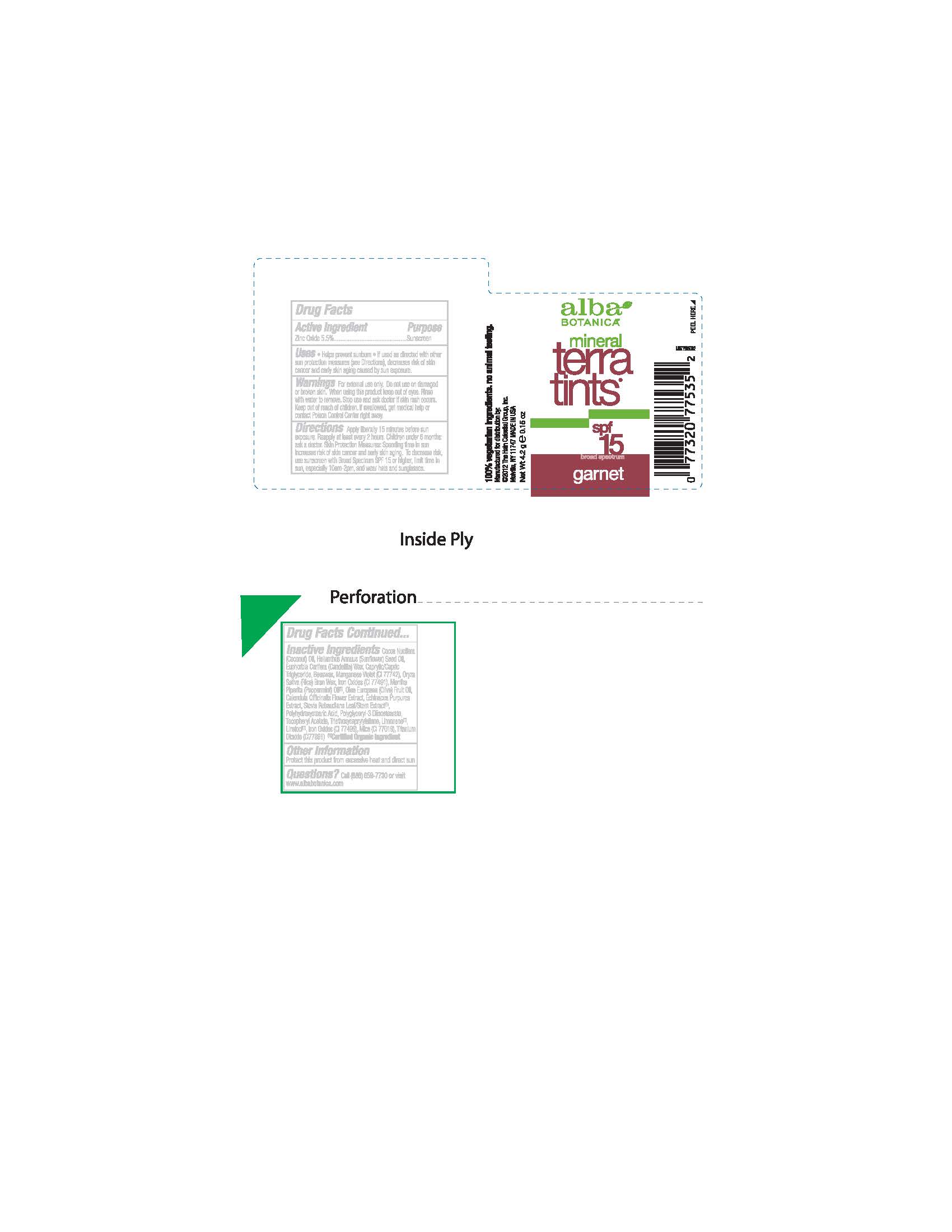 DRUG LABEL: Alba Mineral Terra Tint SPF15 Garnet
NDC: 61995-2535 | Form: CREAM
Manufacturer: The Hain Celestial Group, Inc.
Category: otc | Type: HUMAN OTC DRUG LABEL
Date: 20141008

ACTIVE INGREDIENTS: ZINC OXIDE 5.5 g/100 g
INACTIVE INGREDIENTS: FERROSOFERRIC OXIDE; RICE BRAN; YELLOW WAX; MEDIUM-CHAIN TRIGLYCERIDES; MICA; TITANIUM DIOXIDE; PEPPERMINT OIL; OLIVE OIL; CALENDULA OFFICINALIS FLOWER; ECHINACEA PURPUREA; STEVIA REBAUDIUNA LEAF; POLYHYDROXYSTEARIC ACID (2300 MW); POLYGLYCERYL-3 DIISOSTEARATE; .ALPHA.-TOCOPHEROL ACETATE; TRIETHOXYCAPRYLYLSILANE; FERRIC OXIDE RED; MANGANESE VIOLET; COCONUT OIL; SUNFLOWER OIL; CANDELILLA WAX

ACTIVE INGREDIENT

Zinc Oxide 5.5%

PURPOSE

Sunscreen

DOSAGE AND ADMINISTRATION

Cream. Apply liberally 15 minutes before sun exposure

WARNINGS

For external use only. Do not use on damaged skin. When using this product keep out of eyes.

INDICATIONS AND USAGE

Helps prevent sunburn. If uses as directed with other sun protection measures, decreases risk of skin cancer and early skin aging caused by sun exposure

Keep out of reach of children. If swallowed get medical help or contact Poison Center right away.

INACTIVE INGREDIENT

Cocos Nucifera (Coconut) Oil, Helianthus Annuus (Sunflower) Seed Oil, Euphorbia Cerifera (Candelilla) Wax, Beeswax, Caprylic/Capric Triglyceride, Mica, Titanium Dioxide, Oryza Sativa (Rice) Bran Wax, Mentha Pipperita (Peppermint) Oil (1), Olea Europaea (Olive) Fruit Oil, Calendula Officinalis Flower Extract, Echinacea Purpurea Extract, Stevia Rebaudiana Leaf/Stem Extract (1), Polyhydroxystearic Acid, Polyglyceryl-3 Diisostearate, Tocopheryl Acetate, Triethoxycaprylylsilane, Iron Oxides (CI 77491), Iron Oxides (CI 77499), Manganese Violet.

(1)-Certified Organic Ingredients.